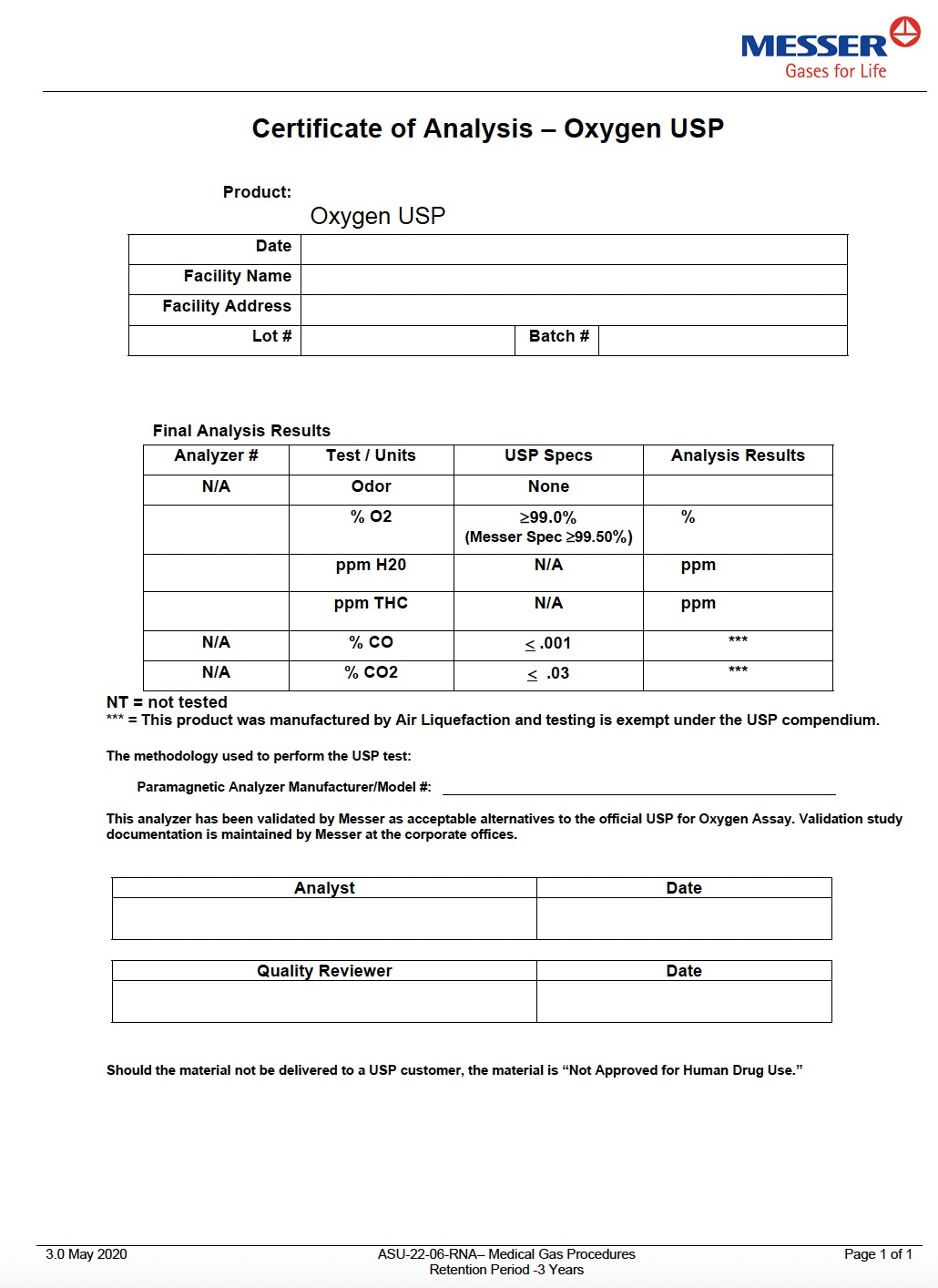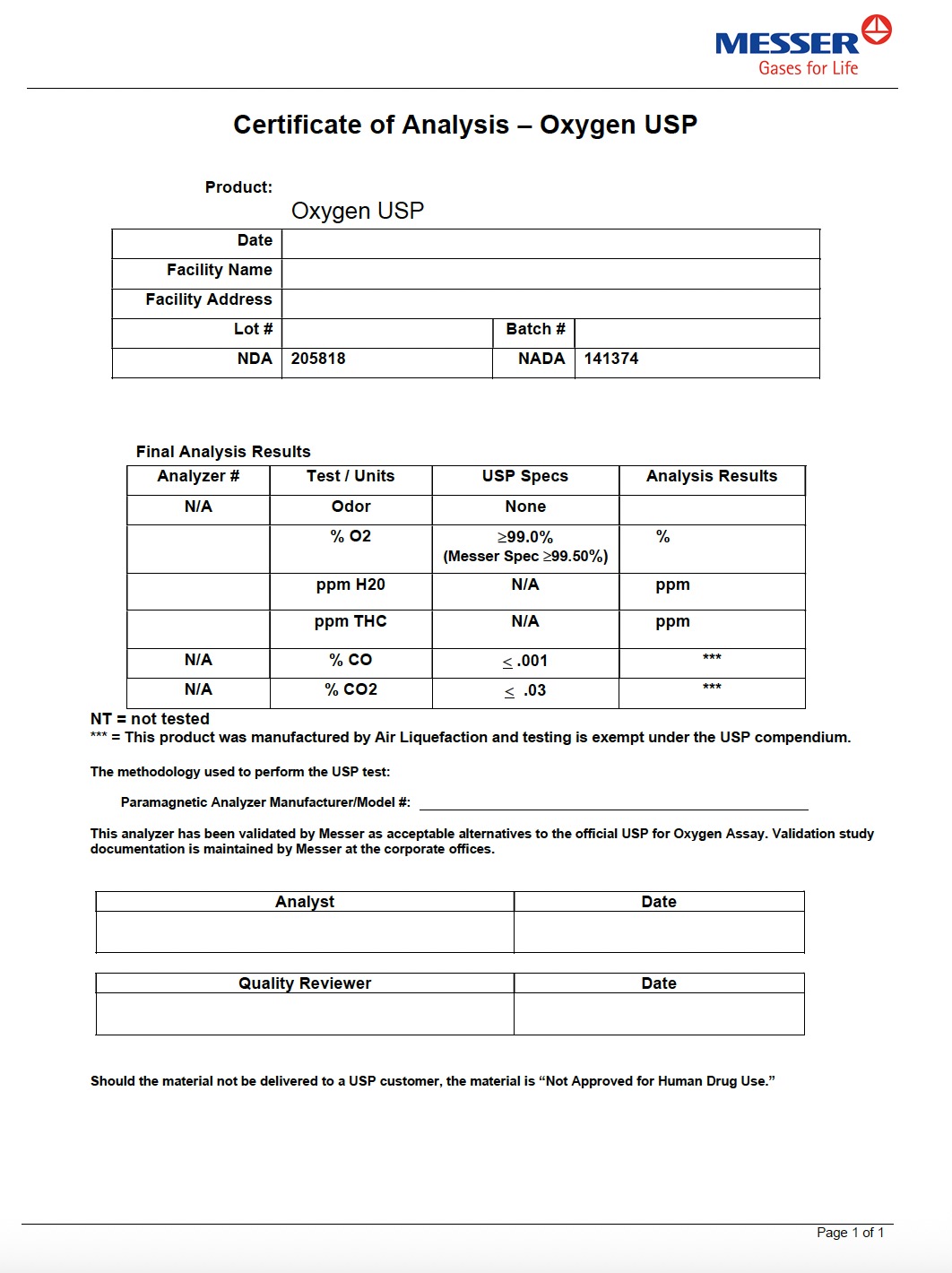 DRUG LABEL: Oxygen
NDC: 52374-911 | Form: GAS
Manufacturer: Messer Gas Puerto Rico, Inc
Category: animal | Type: PRESCRIPTION ANIMAL DRUG LABEL
Date: 20251209

ACTIVE INGREDIENTS: OXYGEN 995 mL/1 L

Oxygen

PACKAGE LABEL

Certificate of Analysis – Oxygen USP

Product:
Oxygen USP

Date

Facility Name

Facility Address

Lot #

Batch #

Final Analysis Results

Analyzer #

Test / Units

USP Specs

Analysis Results

N/A

Odor

None

% O₂

≥99.0%

%

(Messer Spec ≥99.50%)

ppm H₂O

N/A

ppm

ppm THC

N/A

ppm

N/A

% CO

≤ .001

***

N/A

% CO₂

≤ .03

***

NT = not tested
*** = This product was manufactured by Air Liquefaction and testing is exempt under the USP compendium.

The methodology used to perform the USP test:

Paramagnetic Analyzer Manufacturer/Model #:

This analyzer has been validated by Messer as acceptable alternatives to the official USP for Oxygen Assay.
Validation study documentation is maintained by Messer at the corporate offices.

Analyst

Date

Quality Reviewer

Date

Should the material not be delivered to a USP customer, the material is “Not Approved for Human Drug Use.”

PACKAGE LABEL

Certificate of Analysis – Oxygen USP

Product:
Oxygen USP

Date

Facility Name

Facility Address

Lot #

NDA

205818

Batch #

NADA 141374

Final Analysis Results

Analyzer #

Test / Units

USP Specs

Analysis Results

N/A

Odor

None

% O₂

≥99.0%

%

(Messer Spec ≥99.50%)

ppm H₂O

N/A

ppm

ppm THC

N/A

ppm

N/A

% CO

≤ .001

***

N/A

% CO₂

≤ .03

***

NT = not tested
*** = This product was manufactured by Air Liquefaction and testing is exempt under the USP compendium.

The methodology used to perform the USP test:

Paramagnetic Analyzer Manufacturer/Model #:

This analyzer has been validated by Messer as acceptable alternatives to the official USP for Oxygen Assay.
Validation study documentation is maintained by Messer at the corporate offices.

Analyst

Date

Quality Reviewer

Date

Should the material not be delivered to a USP customer, the material is “Not Approved for Human Drug Use.”